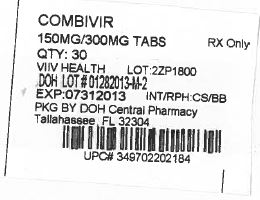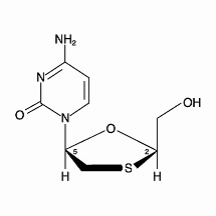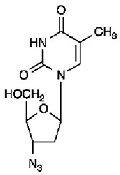 DRUG LABEL: COMBIVIR
NDC: 53808-0895 | Form: TABLET, FILM COATED
Manufacturer: State of Florida DOH Central Pharmacy
Category: prescription | Type: HUMAN PRESCRIPTION DRUG LABEL
Date: 20140227

ACTIVE INGREDIENTS: LAMIVUDINE 150 mg/1 1; ZIDOVUDINE 300 mg/1 1
INACTIVE INGREDIENTS: COLLOIDAL SILICON DIOXIDE; HYPROMELLOSES; MAGNESIUM STEARATE; CELLULOSE, MICROCRYSTALLINE; POLYETHYLENE GLYCOLS; POLYSORBATE 80; SODIUM STARCH GLYCOLATE TYPE A POTATO; TITANIUM DIOXIDE

HIGHLIGHTS OF PRESCRIBING INFORMATION

These highlights do not include all the information needed to use COMBIVIR safely and effectively. See full prescribing information for COMBIVIR.
COMBIVIR (lamivudine and zidovudine) Tablets 150 mg/300 mg
Initial U.S. Approval: 1997

WARNING: HEMATOLOGIC TOXICITY, MYOPATHY, LACTIC ACIDOSIS, EXACERBATIONS OF HEPATITIS B

WARNING: RISK OF HEMATOLOGIC TOXICITY, MYOPATHY, LACTIC ACIDOSIS, EXACERBATIONS OF HEPATITIS B

See full prescribing information for complete boxed warning

- Hematologic toxicity including neutropenia and anemia have been associated with the use of zidovudine, one of the components of COMBIVIR (5.1)
- Symptomatic myopathy associated with prolonged use of zidovudine. (5.2)
- Lactic acidosis and hepatomegaly with steatosis, including fatal cases, have been reported with the use of nucleoside analogues including zidovudine. Suspend treatment if clinical or laboratory findings suggestive of lactic acidosis or pronounced hepatotoxicity occur. (5.3)
- Severe, acute exacerbations of hepatitis B have been reported in patients who are co-infected with hepatitis B virus (HBV) and human immunodeficiency virus (HIV-1) and have discontinued lamivudine, a component of COMBIVIR. Monitor hepatic function closely in these patients and, if appropriate, initiate anti-hepatitis B treatment. (5.4)

1 INDICATIONS AND USAGE

COMBIVIR, a combination of 2 nucleoside analogue reverse transcriptase inhibitors, is indicated in combination with other antiretroviral agents for the treatment of HIV-1 infection. (1)

DOSAGE AND ADMINISTRATION

- Adults and Adolescents weighing ≥30 kg: 1 tablet twice daily. (2.1)
- Pediatrics: Dosage should be based on body weight not to exceed adult doses. (2.2)
- COMBIVIR, a fixed-dose product, should not be prescribed for pediatric patients weighing less than 30 kg or patients requiring dosage adjustment, such as those with renal or hepatic impairment, or patients experiencing dose-limiting adverse reactions. (2.3)

3 DOSAGE FORMS AND STRENGTHS

Tablets: Scored 150 mg lamivudine and 300 mg zidovudine (3)

4 CONTRAINDICATIONS

COMBIVIR Tablets are contraindicated in patients with previously demonstrated clinically significant hypersensitivity (e.g., anaphylaxis, Stevens-Johnson syndrome). (4)

WARNINGS AND PRECAUTIONS

- See boxed warning for information about the following: hematologic toxicity, symptomatic myopathy, lactic acidosis and severe hepatomegaly, and severe acute exacerbations of hepatitis B. (5.1, 5.2, 5.3. 5.4)
- COMBIVIR should not be administered with other lamivudine- or zidovudine-containing products or emtricitabine-containing products. (5.5)
- Hepatic decompensation, some fatal, has occurred in HIV-1/HCV co-infected patients receiving combination antiretroviral therapy and interferon alfa with/without ribavirin. Discontinue COMBIVIR as medically appropriate and consider dose reduction or discontinuation of interferon alfa, ribavirin, or both. (5.6)
- Exacerbation of anemia has been reported in HIV-1/HCV co-infected patients receiving ribavirin and zidovudine. Co-administration of ribavirin and zidovudine is not advised. (5.6)
- Pancreatitis: Use with caution in pediatric patients with a history of pancreatitis or other significant risk factors for pancreatitis. Discontinue treatment as clinically appropriate. (5.7)
- Immune reconstitution syndrome (5.8) and redistribution/accumulation of body fat (5.9) have been reported in patients treated with combination antiretroviral therapy.

6 ADVERSE REACTIONS

- Most commonly reported adverse reactions (incidence greater than or equal to 15%) in adult and pediatric HIV-1 clinical trials of combination lamivudine and zidovudine were headache, nausea, malaise and fatigue, nasal signs and symptoms, diarrhea, and cough. (6.1)

To report SUSPECTED ADVERSE REACTIONS, contact ViiV Healthcare at 1-877-844-8872 or FDA at 1-800-FDA-1088 or www.fda.gov/medwatch.

7 DRUG INTERACTIONS

- Concomitant use with the following drugs should be avoided: stavudine (7.1), zalcitabine (7.1), doxorubicin (7.2).
- Bone marrow suppressive/cytotoxic agents: May increase the hematologic toxicity of zidovudine. (7.3)

USE IN SPECIFIC POPULATIONS

- Pregnancy: Physicians are encouraged to register patients in the Antiretroviral Pregnancy Registry by calling 1-800-258-4263. (8.1)
- Nursing Mothers: HIV-1 infected mothers in the United States should not breastfeed to avoid potential postnatal transmission of HIV-1. (8.3)

FULL PRESCRIBING INFORMATION

WARNING: HEMATOLOGIC TOXICITY, MYOPATHY, LACTIC ACIDOSIS, EXACERBATIONS OF HEPATITIS B

Hematologic Toxicity: Zidovudine, one of the 2 active ingredients in COMBIVIR® (lamivudine and zidovudine) Tablets, has been associated with hematologic toxicity including neutropenia and anemia, particularly in patients with advanced HIV-1 disease [see Warnings and Precautions (5.1)].

Myopathy: Prolonged use of zidovudine has been associated with symptomatic myopathy [see Warnings and Precautions (5.2)].

Lactic Acidosis and Severe Hepatomegaly: Lactic acidosis and hepatomegaly with steatosis, including fatal cases, have been reported with the use of nucleoside analogues alone or in combination, including lamivudine, zidovudine, and other antiretrovirals. Suspend treatment if clinical or laboratory findings suggestive of lactic acidosis or pronounced hepatotoxicity occur[see Warnings and Precautions (5.3)].

Exacerbations of Hepatitis B: Severe, acute exacerbations of hepatitis B have been reported in patients who are co-infected with hepatitis B virus (HBV) and HIV-1 and have discontinued lamivudine, which is one component of COMBIVIR. Hepatic function should be monitored closely with both clinical and laboratory follow-up for at least several months in patients who discontinue COMBIVIR and are co-infected with HIV-1 and HBV. If appropriate, initiation of anti-hepatitis B therapy may be warranted [see Warnings and Precautions (5.4)].

1 INDICATIONS AND USAGE

COMBIVIR, a combination of 2 nucleoside analogues, is indicated in combination with other antiretrovirals for the treatment of HIV-1 infection.

DOSAGE AND ADMINISTRATION

2.1 Adults and Adolescents Weighing ≥30 kg

The recommended oral dose of COMBIVIR in HIV-1-infected adults and adolescents weighing greater than or equal to 30 kg is 1 tablet (containing 150 mg of lamivudine and 300 mg of zidovudine) twice daily.

2.2 Pediatric Patients

The recommended oral dosage of scored COMBIVIR Tablets for pediatric patients who weigh greater than or equal to 30 kg and for whom a solid oral dosage form is appropriate is 1 tablet administered twice daily.

Before prescribing COMBIVIR Tablets, children should be assessed for the ability to swallow tablets. If a child is unable to reliably swallow a COMBIVIR Tablet, the liquid oral formulations should be prescribed: EPIVIR® (lamivudine) Oral Solution and RETROVIR® (zidovudine) Syrup.

2.3 Patients Requiring Dosage Adjustment

Because COMBIVIR is a fixed-dose combination tablet, it should not be prescribed for pediatric patients weighing less than 30 kg or patients requiring dosage adjustment, such as those with reduced renal function (creatinine clearance less than 50 mL/min), patients with hepatic impairment, or patients experiencing dose-limiting adverse reactions. Liquid and solid oral formulations of the individual components of COMBIVIR are available for these populations.

3 DOSAGE FORMS AND STRENGTHS

COMBIVIR Tablets contain 150 mg of lamivudine and 300 mg of zidovudine. The tablets are white, scored, film-coated, modified capsule-shaped tablets, debossed on both tablet faces, such that when broken in half, the full “GX FC3” code is present on both halves of the tablet (“GX” on one face and “FC3” on the opposite face of the tablet).

4 CONTRAINDICATIONS

COMBIVIR Tablets are contraindicated in patients with previously demonstrated clinically significant hypersensitivity (e.g., anaphylaxis, Stevens-Johnson syndrome) to any of the components of the product.

WARNINGS AND PRECAUTIONS

5.1 Hemotologic Toxicity/Bone Marrow Suppression

Zidovudine, a component of COMBIVIR, has been associated with hematologic toxicity including neutropenia and anemia, particularly in patients with advanced HIV-1 disease. COMBIVIR should be used with caution in patients who have bone marrow compromise evidenced by granulocyte count less than 1,000 cells/mm^3 or hemoglobin less than 9.5 g/dL [see Adverse Reactions (6.1)].

Frequent blood counts are strongly recommended in patients with advanced HIV-1 disease who are treated with COMBIVIR. Periodic blood counts are recommended for other HIV-1-infected patients. If anemia or neutropenia develops, dosage interruption may be needed.

5.2 Myopathy

Myopathy and myositis, with pathological changes similar to that produced by HIV-1 disease, have been associated with prolonged use of zidovudine, and therefore may occur with therapy with COMBIVIR.

5.3 Lactic Acidosis/Hepatomegaly With Steatosis

Lactic acidosis and hepatomegaly with steatosis, including fatal cases, have been reported with the use of nucleoside analogues alone or in combination, including lamivudine, zidovudine, and other antiretrovirals. A majority of these cases have been in women. Obesity and prolonged nucleoside exposure may be risk factors. Particular caution should be exercised when administering COMBIVIR to any patient with known risk factors for liver disease; however, cases have also been reported in patients with no known risk factors. Treatment with COMBIVIR should be suspended in any patient who develops clinical or laboratory findings suggestive of lactic acidosis or pronounced hepatotoxicity (which may include hepatomegaly and steatosis even in the absence of marked transaminase elevations).

5.4 Patients With HIV-1 and Hepatitis B Virus Co-infection

Posttreatment Exacerbations of Hepatitis: In clinical trials in non-HIV-1-infected patients treated with lamivudine for chronic HBV, clinical and laboratory evidence of exacerbations of hepatitis have occurred after discontinuation of lamivudine. These exacerbations have been detected primarily by serum ALT elevations in addition to re-emergence of hepatitis B viral DNA (HBV DNA). Although most events appear to have been self-limited, fatalities have been reported in some cases. Similar events have been reported from post-marketing experience after changes from lamivudine-containing HIV-1 treatment regimens to non-lamivudine-containing regimens in patients infected with both HIV-1 and HBV. The causal relationship to discontinuation of lamivudine treatment is unknown. Patients should be closely monitored with both clinical and laboratory follow-up for at least several months after stopping treatment. There is insufficient evidence to determine whether re-initiation of lamivudine alters the course of posttreatment exacerbations of hepatitis.

Important Differences Among Lamivudine-Containing Products: COMBIVIR Tablets contain a higher dose of the same active ingredient (lamivudine) than EPIVIR-HBV® (lamivudine) Tablets and Oral Solution. EPIVIR-HBV was developed for treating chronic hepatitis B. Safety and efficacy of lamivudine have not been established for treatment of chronic hepatitis B in patients co-infected with HIV-1 and HBV.

Emergence of Lamivudine-Resistant HBV: In non-HIV-infected patients treated with lamivudine for chronic hepatitis B, emergence of lamivudine-resistant HBV has been detected and has been associated with diminished treatment response (see full prescribing information for EPIVIR-HBV for additional information). Emergence of hepatitis B virus variants associated with resistance to lamivudine has also been reported in HIV-1-infected patients who have received lamivudine-containing antiretroviral regimens in the presence of concurrent infection with hepatitis B virus.

5.5 Use With Other, Lamivudine-, Zidovudine-, and/or Emtricitabine-Containing Products

COMBIVIR is a fixed-dose combination of lamivudine and zidovudine. COMBIVIR should not be administered concomitantly with other lamivudine- or zidovudine-containing products including EPIVIR® (lamivudine) Tablets and Oral Solution; EPIVIR-HBV Tablets and Oral Solution; RETROVIR® (zidovudine) Tablets, Capsules, Syrup, and IV Infusion; EPZICOM® (abacavir sulfate and lamivudine) Tablets; or TRIZIVIR® (abacavir sulfate, lamivudine, and zidovudine) Tablets; or emtricitabine-containing products, including ATRIPLA® (efavirenz, emtricitabine, and tenofovir), EMTRIVA® (emtricitabine), TRUVADA® (emtricitabine and tenofovir), or COMPLERA® (rilpivirine/emtricitabine/tenofovir).

5.6 Use With Interferon- and Ribavirin-Based Regimens

In vitro studies have shown ribavirin can reduce the phosphorylation of pyrimidine nucleoside analogues such as lamivudine and zidovudine. Although no evidence of a pharmacokinetic or pharmacodynamic interaction (e.g., loss of HIV-1/HCV virologic suppression) was seen when ribavirin was coadministered with lamivudine or zidovudine in HIV-1/HCV co-infected patients [see Clinical Pharmacology (12.3)], hepatic decompensation (some fatal) has occurred in HIV-1/HCV co-infected patients receiving combination antiretroviral therapy for HIV-1 and interferon alfa with or without ribavirin. Patients receiving interferon alfa with or without ribavirin and COMBIVIR should be closely monitored for treatment-associated toxicities, especially hepatic decompensation, neutropenia, and anemia. Discontinuation of COMBIVIR should be considered as medically appropriate. Dose reduction or discontinuation of interferon alfa, ribavirin, or both should also be considered if worsening clinical toxicities are observed, including hepatic decompensation (e.g., Child-Pugh greater than 6) (see the complete prescribing information for interferon and ribavirin).

Exacerbation of anemia has been reported in HIV-1/HCV co-infected patients receiving ribavirin and zidovudine. Coadministration of ribavirin and zidovudine is not advised.

5.7 Pancreatitis

COMBIVIR should be used with caution in patients with a history of pancreatitis or other significant risk factors for the development of pancreatitis. Treatment with COMBIVIR should be stopped immediately if clinical signs, symptoms, or laboratory abnormalities suggestive of pancreatitis occur [see Adverse Reactions (6.1)].

5.8 Immune Reconstitution Syndrome

Immune reconstitution syndrome has been reported in patients treated with combination antiretroviral therapy, including COMBIVIR. During the initial phase of combination antiretroviral treatment, patients whose immune systems respond may develop an inflammatory response to indolent or residual opportunistic infections (such as Mycobacterium avium infection, cytomegalovirus, Pneumocystis jirovecii pneumonia [PCP], or tuberculosis), which may necessitate further evaluation and treatment.

Autoimmune disorders (such as Graves’ disease, polymyositis, and Guillain-Barré syndrome) have also been reported to occur in the setting of immune reconstitution; however, the time to onset is more variable, and can occur many months after initiation of treatment.

5.9 Fat Redistribution

Redistribution/accumulation of body fat including central obesity, dorsocervical fat enlargement (buffalo hump), peripheral wasting, facial wasting, breast enlargement, and “cushingoid appearance” have been observed in patients receiving antiretroviral therapy. The mechanism and long-term consequences of these events are currently unknown. A causal relationship has not been established.

6 ADVERSE REACTIONS

The following adverse reactions are discussed in greater detail in other sections of the labeling:

- Hematologic toxicity, including neutropenia and anemia [see Boxed Warning, Warnings and Precautions (5.1)].
- Symptomatic myopathy [see Boxed Warning, Warnings and Precautions (5.2)].
- Lactic acidosis and hepatomegaly with steatosis [see Boxed Warning, Warnings and Precautions (5.3)].
- Acute exacerbations of hepatitis B [see Boxed Warning, Warnings and Precautions (5.4)].
- Hepatic decompensation in patients co-infected with HIV-1 and hepatitis C [see Warnings and Precautions (5.6)].
- Exacerbation of anemia in HIV-1/HCV co-infected patients receiving ribavirin and zidovudine [see Warnings and Precautions (5.6)].
- Pancreatitis [see Warnings and Precautions (5.7)].

6.1 Clinical Trials Experience

Because clinical trials are conducted under widely varying conditions, adverse reaction rates observed in the clinical trials of a drug cannot be directly compared with rates in the clinical trials of another drug and may not reflect the rates observed in practice.

Lamivudine Plus Zidovudine Administered As Separate Formulations: In 4 randomized, controlled trials of EPIVIR 300 mg per day plus RETROVIR 600 mg per day, the following selected adverse reactions and laboratory abnormalities were observed (see Tables 1 and 2).

Table 1. Selected Clinical Adverse Reactions (≥5% Frequency) in 4 Controlled Clinical Trials With EPIVIR 300 mg/day and RETROVIR 600 mg/day
Adverse Reaction | EPIVIR plus RETROVIR; (n = 251)
Body as a whole
Headache | 35%
Malaise & fatigue | 27%
Fever or chills | 10%
Digestive
Nausea | 33%
Diarrhea | 18%
Nausea & vomiting | 13%
Anorexia and/or decreased appetite | 10%
Abdominal pain | 9%
Abdominal cramps | 6%
Dyspepsia | 5%
Nervous system
Neuropathy | 12%
Insomnia & other sleep disorders | 11%
Dizziness | 10%
Depressive disorders | 9%
Respiratory
Nasal signs & symptoms | 20%
Cough | 18%
Skin
Skin rashes | 9%
Musculoskeletal
Musculoskeletal pain | 12%
Myalgia | 8%
Arthralgia | 5%

Pancreatitis was observed in 9 of the 2,613 adult subjects (0.3%) who received EPIVIR in controlled clinical trials [see Warnings and Precautions (5.7)].

Selected laboratory abnormalities observed during therapy are listed in Table 2.

Table 2. Frequencies of Selected Laboratory Abnormalities Among Adults in 4 Controlled Clinical Trials of EPIVIR 300 mg/day plus RETROVIR 600 mg/daya
Test; (Abnormal Level) | EPIVIR plus RETROVIR; % (n)
Neutropenia (ANC<750/mm^3) | 7.2% (237)
Anemia (Hgb<8.0 g/dL) | 2.9% (241)
Thrombocytopenia (platelets<50,000/mm^3) | 0.4% (240)
ALT (>5.0 x ULN) | 3.7% (241)
AST (>5.0 x ULN) | 1.7% (241)
Bilirubin (>2.5 x ULN) | 0.8% (241)
Amylase (>2.0 x ULN) | 4.2% (72)
ULN = Upper limit of normal.
ANC = Absolute neutrophil count.
n = Number of subjects assessed.
a Frequencies of these laboratory abnormalities were higher in subjects with mild laboratory abnormalities at baseline.

6.2 Postmarketing Experience

In addition to adverse reactions reported from clinical trials, the following reactions have been identified during post-approval use of EPIVIR, RETROVIR, and/or COMBIVIR. Because they are reported voluntarily from a population of unknown size, estimates of frequency cannot be made. These events have been chosen for inclusion due to a combination of their seriousness, frequency of reporting, or potential causal connection to EPIVIR, RETROVIR, and/or COMBIVIR.

Body as a Whole: Redistribution/accumulation of body fat [see Warnings and Precautions (5.9)].

Cardiovascular: Cardiomyopathy.

Endocrine and Metabolic: Gynecomastia, hyperglycemia.

Gastrointestinal: Oral mucosal pigmentation, stomatitis.

General: Vasculitis, weakness.

Hemic and Lymphatic: Anemia, (including pure red cell aplasia and anemias progressing on therapy), lymphadenopathy, splenomegaly.

Hepatic and Pancreatic: Lactic acidosis and hepatic steatosis, pancreatitis, posttreatment exacerbation of hepatitis B [see Boxed Warning, Warnings and Precautions (5.3), (5.4), (5.7)].

Hypersensitivity: Sensitization reactions (including anaphylaxis), urticaria.

Musculoskeletal: Muscle weakness, CPK elevation, rhabdomyolysis.

Nervous: Paresthesia, peripheral neuropathy, seizures.

Respiratory: Abnormal breath sounds/wheezing.

Skin: Alopecia, erythema multiforme, Stevens-Johnson syndrome.

7 DRUG INTERACTIONS

No drug interaction trials have been conducted using COMBIVIR Tablets [see Clinical Pharmacology (12.3)].

7.1 Antiretroviral Agents

Lamivudine: Zalcitabine: Lamivudine and zalcitabine may inhibit the intracellular phosphorylation of one another. Therefore, use of COMBIVIR in combination with zalcitabine is not recommended.

Zidovudine: Stavudine: Concomitant use of COMBIVIR with stavudine should be avoided since an antagonistic relationship with zidovudine has been demonstrated in vitro.

Nucleoside Analogues Affecting DNA Replication: Some nucleoside analogues affecting DNA replication, such as ribavirin, antagonize the in vitro antiviral activity of zidovudine against HIV-1; concomitant use of such drugs should be avoided.

7.2 Doxorubicin

Zidovudine: Concomitant use of COMBIVIR with doxorubicin should be avoided since an antagonistic relationship with zidovudine has been demonstrated in vitro.

7.3 Hematologic/Bone Marrow Suppressive/Cytotoxic Agents

Zidovudine: Coadministration of ganciclovir, interferon alfa, ribavirin, and other bone marrow suppressive or cytotoxic agents may increase the hematologic toxicity of zidovudine.

7.4 Interferon- and Ribavirin-Based Regimens

Lamivudine: Although no evidence of a pharmacokinetic or pharmacodynamic interaction (e.g., loss of HIV-1/HCV virologic suppression) was seen when ribavirin was coadministered with lamivudine in HIV-1/HCV co-infected patients, hepatic decompensation (some fatal) has occurred in HIV-1/HCV co-infected patients receiving combination antiretroviral therapy for HIV-1 and interferon alfa with or without ribavirin [see Warnings and Precautions (5.5), Clinical Pharmacology (12.3)].

7.5 Trimethoprim/Sulfamethoxazole (TMP/SMX)

Lamivudine: No change in dose of either drug is recommended. There is no information regarding the effect on lamivudine pharmacokinetics of higher doses of TMP/SMX such as those used to treat PCP.

USE IN SPECIFIC POPULATIONS

8.1 Pregnancy

Pregnancy Category C.

Fetal Risk Summary: There are no adequate and well-controlled trials of COMBIVIR (lamivudine and zidovudine) in pregnant women. Clinical trial data demonstrate that maternal zidovudine treatment during pregnancy reduces vertical transmission of HIV-1 infection to the fetus. Animal reproduction studies performed with lamivudine and zidovudine showed increased embryotoxicity and fetal malformations (zidovudine), and increased embryolethality (lamivudine). COMBIVIR should be used during pregnancy only if the potential benefit justifies the potential risk to the fetus.

Antiretroviral Pregnancy Registry: To monitor maternal-fetal outcomes of pregnant women exposed to COMBIVIR and other antiretroviral agents, an Antiretroviral Pregnancy Registry has been established. Physicians are encouraged to register patients by calling 1-800-258-4263.

Clinical Considerations: Treatment of HIV during pregnancy optimizes the health of both mother and fetus. Clinical trial data reviewed by FDA demonstrate that maternal zidovudine treatment significantly reduces vertical transmission of HIV-1 infection to the fetus [see Clinical Studies (14.2)]. Published data suggest that combination antiretroviral regimens may reduce the rate of vertical transmission even further.

Pharmacokinetics of lamivudine and zidovudine in pregnant women are similar to the pharmacokinetics in nonpregnant women. No dose adjustments are needed during pregnancy.

In a clinical trial, adverse events among HIV-1-infected women were not different among untreated women and women treated with zidovudine. It is not known whether risks of adverse events associated with lamivudine are altered in pregnant women compared with other HIV-1-infected patients (see Human data below).

Data: Human Data: Lamivudine: Lamivudine pharmacokinetics were studied in pregnant women during 2 clinical trials conducted in South Africa. The trial assessed pharmacokinetics in: 16 women at 36 weeks gestation using 150 mg lamivudine twice daily with zidovudine, 10 women at 38 weeks gestation using 150 mg lamivudine twice daily with zidovudine, and 10 women at 38 weeks gestation using lamivudine 300 mg twice daily without other antiretrovirals. Lamivudine pharmacokinetics in pregnant women were similar to those seen in nonpregnant adults and in postpartum women. Lamivudine concentrations were generally similar in maternal, neonatal, and umbilical cord serum samples.

Zidovudine: A randomized, double-blind, placebo-controlled trial was conducted in HIV-1-infected pregnant women to determine the utility of zidovudine for the prevention of maternal-fetal HIV-1 transmission. Zidovudine treatment during pregnancy reduced the rate of maternal-fetal HIV-1 transmission from 24.9% for infants born to placebo-treated mothers to 7.8% for infants born to mothers treated with zidovudine. There were no differences in pregnancy-related adverse events between the treatment groups. Congenital abnormalities occurred with similar frequency between neonates born to mothers who received zidovudine and neonates born to mothers who received placebo. The observed abnormalities included problems in embryogenesis (prior to 14 weeks) or were recognized on ultrasound before or immediately after initiation of trial drug [see Clinical Studies (14.2)].

Zidovudine pharmacokinetics were studied in a Phase 1 trial of 8 women during the last trimester of pregnancy. As pregnancy progressed, there was no evidence of drug accumulation. The pharmacokinetics of zidovudine were similar to that of nonpregnant adults. Consistent with passive transmission of the drug across the placenta, zidovudine concentrations in neonatal plasma at birth were essentially equal to those in maternal plasma at delivery.

Animal Data: Lamivudine: Animal reproduction studies performed at oral doses up to 130 and 60 times the adult dose in rats and rabbits, respectively, revealed no evidence of teratogenicity due to lamivudine. Increased early embryolethality occurred in rabbits at exposure levels similar to those in humans. However, there was no indication of this effect in rats at exposure levels up to 35 times those in humans. Based on animal studies, lamivudine crosses the placenta and is transferred to the fetus [see Nonclinical Toxicology (13.2)].

Zidovudine: Increased fetal resorptions occurred in pregnant rats and rabbits treated with doses of zidovudine that produced drug plasma concentrations 66 to 226 times (rats) and 12 to 87 times (rabbits) the mean steady-state peak human plasma concentration following a single 100-mg dose of zidovudine. There were no other reported developmental anomalies. In another developmental toxicity study, pregnant rats received zidovudine up to near-lethal doses that produced peak plasma concentrations 350 times peak human plasma concentrations (300 times the daily exposure [AUC] in humans given 600 mg/day zidovudine). This dose was associated with marked maternal toxicity and an increased incidence of fetal malformations. However, there were no signs of teratogenicity at doses up to one-fifth the lethal dose [see Nonclinical Toxicology(13.2)].

8.3 Nursing Mothers

The Centers for Disease Control and Prevention recommend that HIV-1-infected mothers in the United States not breastfeed their infants to avoid risking postnatal transmission of HIV-1 infection. Because of both the potential for HIV-1 transmission and serious adverse reactions in nursing infants, mothers should be instructed not to breastfeed if they are receiving COMBIVIR.

Although no trials of COMBIVIR excretion in breast milk have been performed, lactation trials performed with lamivudine and zidovudine show that both drugs are excreted in human breast milk. Samples of breast milk obtained from 20 mothers receiving lamivudine monotherapy (300 mg twice daily) or combination therapy (150 mg lamivudine twice daily and 300 mg zidovudine twice daily) had measurable concentrations of lamivudine. In another trial, after administration of a single dose of 200 mg zidovudine to 13 HIV‑1‑infected women, the mean concentration of zidovudine was similar in human milk and serum.

8.4 Pediatric Use

COMBIVIR should not be administered to pediatric patients weighing less than 30 kg, because it is a fixed-dose combination that cannot be adjusted for this patient population.

8.5 Geriatric Use

Clinical trials of COMBIVIR did not include sufficient numbers of subjects aged 65 and over to determine whether they respond differently from younger subjects. In general, dose selection for an elderly patient should be cautious, reflecting the greater frequency of decreased hepatic, renal, or cardiac function, and of concomitant disease or other drug therapy. COMBIVIR is not recommended for patients with impaired renal function (i.e., creatinine clearance less than 50 mL/min) because it is a fixed-dose combination that cannot be adjusted.

8.6 Renal Impairment

Reduction of the dosages of lamivudine and zidovudine is recommended for patients with impaired renal function. Patients with creatinine clearance less than 50 mL/min should not receive COMBIVIR because it is a fixed-dose combination that cannot be adjusted.

8.7 Hepatic Impairment

A reduction in the daily dose of zidovudine may be necessary in patients with mild to moderate impaired hepatic function or liver cirrhosis. COMBIVIR is not recommended for patients with impaired hepatic function because it is a fixed-dose combination that cannot be adjusted.

10 OVERDOSAGE

COMBIVIR: There is no known antidote for COMBIVIR.

Lamivudine: One case of an adult ingesting 6 grams of lamivudine was reported; there were no clinical signs or symptoms noted and hematologic tests remained normal. Because a negligible amount of lamivudine was removed via (4-hour) hemodialysis, continuous ambulatory peritoneal dialysis, and automated peritoneal dialysis, it is not known if continuous hemodialysis would provide clinical benefit in a lamivudine overdose event.

Zidovudine: Acute overdoses of zidovudine have been reported in pediatric patients and adults. These involved exposures up to 50 grams. The only consistent findings were nausea and vomiting. Other reported occurrences included headache, dizziness, drowsiness, lethargy, confusion, and 1 report of a grand mal seizure. Hematologic changes were transient. All patients recovered. Hemodialysis and peritoneal dialysis appear to have a negligible effect on the removal of zidovudine, while elimination of its primary metabolite, 3′-azido-3′-deoxy-5′-O-β-D-glucopyranuronosylthymidine (GZDV), is enhanced.

11 DESCRIPTION

COMBIVIR: COMBIVIR Tablets are combination tablets containing lamivudine and zidovudine. Lamivudine (EPIVIR) and zidovudine (RETROVIR, azidothymidine, AZT, or ZDV) are synthetic nucleoside analogues with activity against HIV-1.

COMBIVIR Tablets are for oral administration. Each film-coated tablet contains 150 mg of lamivudine, 300 mg of zidovudine, and the inactive ingredients colloidal silicon dioxide, hypromellose, magnesium stearate, microcrystalline cellulose, polyethylene glycol, polysorbate 80, sodium starch glycolate, and titanium dioxide.

Lamivudine: The chemical name of lamivudine is (2R,cis)-4-amino-1-(2-hydroxymethyl-1,3-oxathiolan-5-yl)-(1H)-pyrimidin-2-one. Lamivudine is the (-)enantiomer of a dideoxy analogue of cytidine. Lamivudine has also been referred to as (-)2′,3′-dideoxy, 3′-thiacytidine. It has a molecular formula of C8H11N3O3S and a molecular weight of 229.3. It has the following structural formula:

Lamivudine is a white to off-white crystalline solid with a solubility of approximately 70 mg/mL in water at 20°C.

Zidovudine: The chemical name of zidovudine is 3′-azido-3′-deoxythymidine. It has a molecular formula of C10H13N5O4 and a molecular weight of 267.24. It has the following structural formula:

Zidovudine is a white to beige, odorless, crystalline solid with a solubility of 20.1 mg/mL in water at 25°C.

12 CLINICAL PHARMACOLOGY

12.1 Mechanism of Action

COMBIVIR is an antiviral agent [see Clinical Pharmacology (12.4)].

12.3 Pharmacokinetics

Pharmacokinetics in Adults: COMBIVIR: One COMBIVIR Tablet was bioequivalent to 1 EPIVIR Tablet (150 mg) plus 1 RETROVIR Tablet (300 mg) following single-dose administration to fasting healthy subjects (n = 24).

Lamivudine: The pharmacokinetic properties of lamivudine in fasting subjects are summarized in Table 3. Following oral administration, lamivudine is rapidly absorbed and extensively distributed. Binding to plasma protein is low. Approximately 70% of an intravenous dose of lamivudine is recovered as unchanged drug in the urine. Metabolism of lamivudine is a minor route of elimination. In humans, the only known metabolite is the trans-sulfoxide metabolite (approximately 5% of an oral dose after 12 hours).

Zidovudine: The pharmacokinetic properties of zidovudine in fasting subjects are summarized in Table 3. Following oral administration, zidovudine is rapidly absorbed and extensively distributed. Binding to plasma protein is low. Zidovudine is eliminated primarily by hepatic metabolism. The major metabolite of zidovudine is GZDV. GZDV area under the curve (AUC) is about 3-fold greater than the zidovudine AUC. Urinary recovery of zidovudine and GZDV accounts for 14% and 74% of the dose following oral administration, respectively. A second metabolite, 3′-amino-3′-deoxythymidine (AMT), has been identified in plasma. The AMT AUC was one fifth of the zidovudine AUC.

Table 3. Pharmacokinetic Parametersa for Lamivudine and Zidovudine in Adults
Parameter | Lamivudine |  | Zidovudine
Oral bioavailability (%) | 86 ± 16 | N = 12 | 64 ± 10 | n = 5
Apparent volume of distribution (L/kg) | 1.3 ± 0.4 | N = 20 | 1.6 ± 0.6 | n = 8
Plasma protein binding (%) | <36 |  | <38
CSF:plasma ratiob | 0.12 [0.04 to 0.47] | n = 38c | 0.60 [0.04 to 2.62] | N = 39d
Systemic clearance (L/hr/kg) | 0.33 ± 0.06 | N = 20 | 1.6 ± 0.6 | n = 6
Renal clearance (L/hr/kg) | 0.22 ± 0.06 | N = 20 | 0.34 ± 0.05 | n = 9
Elimination half-life (hr)e | 5 to 7 |  | 0.5 to 3
a Data presented as mean ± standard deviation except where noted.
b Median [range].
c Children.
d Adults.
e Approximate range.

Effect of Food on Absorption of COMBIVIR: COMBIVIR may be administered with or without food. The lamivudine and zidovudine AUC following administration of COMBIVIR with food was similar when compared with fasting healthy subjects (n = 24).

Special Populations:

Pregnancy: See Use in Specific Populations (8.1).

COMBIVIR: No data are available.

Zidovudine: Zidovudine pharmacokinetics has been studied in a Phase 1 trial of 8 women during the last trimester of pregnancy. As pregnancy progressed, there was no evidence of drug accumulation. The pharmacokinetics of zidovudine was similar to that of nonpregnant adults. Consistent with passive transmission of the drug across the placenta, zidovudine concentrations in neonatal plasma at birth were essentially equal to those in maternal plasma at delivery. Although data are limited, methadone maintenance therapy in 5 pregnant women did not appear to alter zidovudine pharmacokinetics. In a nonpregnant adult population, a potential for interaction has been identified.

Nursing Mothers: See Use in Specific Populations (8.3).

Pediatric Patients: COMBIVIR should not be administered to pediatric patients weighing less than 30 kg.

Geriatric Patients: The pharmacokinetics of lamivudine and zidovudine have not been studied in patients over 65 years of age.

Gender: A pharmacokinetic trial in healthy male (n = 12) and female (n = 12) subjects showed no gender differences in zidovudine AUC∞ or lamivudine AUC∞ normalized for body weight.

Race: Lamivudine: There are no significant racial differences in lamivudine pharmacokinetics.

Zidovudine: The pharmacokinetics of zidovudine with respect to race have not been determined.

Drug Interactions: See Drug Interactions (7).

No drug interaction trials have been conducted using COMBIVIR Tablets. However, Table 4 presents drug interaction information for the individual components of COMBIVIR.

Lamivudine Plus Zidovudine: No clinically significant alterations in lamivudine or zidovudine pharmacokinetics were observed in 12 asymptomatic HIV-1-infected adult subjects given a single dose of zidovudine (200 mg) in combination with multiple doses of lamivudine (300 mg q 12 hr).

Table 4. Effect of Coadministered Drugs on Lamivudine and Zidovudine AUCa
Note: ROUTINE DOSE MODIFICATION OF LAMIVUDINE AND ZIDOVUDINE IS NOT WARRANTED WITH COADMINISTRATION OF THE FOLLOWING DRUGS.
Drugs That May Alter Lamivudine Blood Concentrations
Coadministered Drug and Dose | Lamivudine Dose | n | Lamivudine; Concentrations |  | Concentration of Coadministered Drug
Coadministered Drug and Dose | Lamivudine Dose | n | AUC | Variability | Concentration of Coadministered Drug
Nelfinavir; 750 mg q 8 hr x 7 to 10 days | single 150 mg | 11 | ↑AUC 10% | 95% CI:; 1% to 20% | ↔
Trimethoprim 160 mg/Sulfamethoxazole; 800 mg daily x 5 days | single 300 mg | 14 | ↑AUC 43% | 90% CI:; 32% to 55% | ↔
Drugs That May Alter Zidovudine Blood Concentrations
Coadministered Drug and Dose | Zidovudine Dose | n | Zidovudine; Concentrations |  | Concentration of Coadministered Drug
Coadministered Drug and Dose | Zidovudine Dose | n | AUC | Variability | Concentration of Coadministered Drug
Atovaquone; 750 mg q 12 hr with food | 200 mg q 8 hr | 14 | ↑AUC 31% | Range; 23% to 78%b | ↔
Clarithromycin; 500 mg twice daily | 100 mg q 4 hr x 7 days | 4 | ↓AUC 12% | Range; ↓34% to ↑14% | Not Reported
Fluconazole; 400 mg daily | 200 mg q 8 hr | 12 | ↑AUC 74% | 95% CI:; 54% to 98% | Not Reported
Methadone; 30 to 90 mg daily | 200 mg q 4 hr | 9 | ↑AUC 43% | Range; 16% to 64%b | ↔
Nelfinavir; 750 mg q 8 hr x 7 to 10 days | single 200 mg | 11 | ↓AUC 35% | Range; 28% to 41% | ↔
Probenecid; 500 mg q 6 hr x 2 days | 2 mg/kg q 8 hr x 3 days | 3 | ↑AUC 106% | Range; 100% to 170%b | Not Assessed
Rifampin; 600 mg daily x 14 days | 200 mg q 8 hr; X 14 days | 8 | ↓AUC; 47% | 90% CI:; 41% to 53% | Not Assessed
Ritonavir; 300 mg q 6 hr x 4 days | 200 mg q 8 hr x 4 days | 9 | ↓AUC 25% | 95% CI:; 15% to 34% | ↔
Valproic acid; 250 mg or 500 mg q 8 hr x 4 days | 100 mg q 8 hr x 4 days | 6 | ↑AUC 80% | Range; 64% to 130%b | Not Assessed
↑ = Increase; ↓= Decrease; ↔ = no significant change; AUC = area under the concentration versus time curve; CI = confidence interval.
a This table is not all inclusive.
b Estimated range of percent difference.

Ribavirin: In vitro data indicate ribavirin reduces phosphorylation of lamivudine, stavudine, and zidovudine. However, no pharmacokinetic (e.g., plasma concentrations or intracellular triphosphorylated active metabolite concentrations) or pharmacodynamic (e.g., loss of HIV-1/HCV virologic suppression) interaction was observed when ribavirin and lamivudine (n = 18), stavudine (n = 10), or zidovudine (n = 6) were coadministered as part of a multi-drug regimen to HIV-1/HCV co-infected subjects [see Warnings and Precautions (5.5)].

12.4 Microbiology

Mechanism of Action: Lamivudine: Intracellularly, lamivudine is phosphorylated to its active 5′-triphosphate metabolite, lamivudine triphosphate (3TC-TP). The principal mode of action of 3TC-TP is inhibition of reverse transcriptase (RT) via DNA chain termination after incorporation of the nucleotide analogue. 3TC-TP is a weak inhibitor of cellular DNA polymerases α, β, and γ.

Zidovudine: Intracellularly, zidovudine is phosphorylated to its active 5′-triphosphate metabolite, zidovudine triphosphate (ZDV-TP). The principal mode of action of ZDV-TP is inhibition of RT via DNA chain termination after incorporation of the nucleotide analogue. ZDV-TP is a weak inhibitor of the cellular DNA polymerases α and γ and has been reported to be incorporated into the DNA of cells in culture.

Antiviral Activity: Lamivudine Plus Zidovudine: In HIV-1–infected MT-4 cells, lamivudine in combination with zidovudine at various ratios exhibited synergistic antiretroviral activity.

Lamivudine: The antiviral activity of lamivudine against HIV-1 was assessed in a number of cell lines (including monocytes and fresh human peripheral blood lymphocytes) using standard susceptibility assays. EC50 values (50% effective concentrations) were in the range of 0.003 to 15 μM (1 μM = 0.23 mcg/mL). HIV-1 from therapy-naive subjects with no amino acid substitutions associated with resistance gave median EC50 values of 0.429 µM (range: 0.200 to 2.007 µM) from Virco (n = 92 baseline samples from COL40263) and 2.35 µM (1.37 to 3.68 µM) from Monogram Biosciences (n = 135 baseline samples from ESS30009). The EC50 values of lamivudine against different HIV-1 clades (A-G) ranged from 0.001 to 0.120 µM, and against HIV-2 isolates from 0.003 to 0.120 μM in peripheral blood mononuclear cells. Ribavirin (50 μM) decreased the anti-HIV-1 activity of lamivudine by 3.5 fold in MT-4 cells.

Zidovudine: The antiviral activity of zidovudine against HIV-1 was assessed in a number of cell lines (including monocytes and fresh human peripheral blood lymphocytes). The EC50 and EC90 values for zidovudine were 0.01 to 0.49 µM (1 μM = 0.27 mcg/mL) and 0.1 to 9 μM, respectively. HIV-1 from therapy-naive subjects with no amino acid substitutions associated with resistance gave median EC50 values of 0.011 µM (range: 0.005 to 0.110 µM) from Virco (n = 92 baseline samples from COL40263) and 0.0017 µM (0.006 to 0.0340 µM) from Monogram Biosciences (n = 135 baseline samples from ESS30009). The EC50 values of zidovudine against different HIV-1 clades (A-G) ranged from 0.00018 to 0.02 μM, and against HIV-2 isolates from 0.00049 to 0.004 μM. In cell culture drug combination studies, zidovudine demonstrates synergistic activity with the nucleoside reverse transcriptase inhibitors (NRTIs) abacavir, didanosine, lamivudine, and zalcitabine; the non-nucleoside reverse transcriptase inhibitors (NNRTIs) delavirdine and nevirapine; and the protease inhibitors (PIs) indinavir, nelfinavir, ritonavir, and saquinavir; and additive activity with interferon alfa. Ribavirin has been found to inhibit the phosphorylation of zidovudine in cell culture.

Resistance: Lamivudine Plus Zidovudine Administered As Separate Formulations: In subjects receiving lamivudine monotherapy or combination therapy with lamivudine plus zidovudine, HIV‑1 isolates from most subjects became phenotypically and genotypically resistant to lamivudine within 12 weeks. In some subjects harboring zidovudine‑resistant virus at baseline, phenotypic sensitivity to zidovudine was restored by 12 weeks of treatment with lamivudine and zidovudine. Combination therapy with lamivudine plus zidovudine delayed the emergence of amino acid substitutions conferring resistance to zidovudine.

HIV-1 strains resistant to both lamivudine and zidovudine have been isolated from subjects after prolonged lamivudine/zidovudine therapy. Dual resistance required the presence of multiple amino acid substitutions, the most essential of which may be G333E. The incidence of dual resistance and the duration of combination therapy required before dual resistance occurs are unknown.

Lamivudine: Lamivudine‑resistant isolates of HIV‑1 have been selected in cell culture and have also been recovered from subjects treated with lamivudine or lamivudine plus zidovudine. Genotypic analysis of isolates selected in cell culture and recovered from lamivudine‑treated subjects showed that the resistance was due to a specific amino acid substitution in the HIV‑1 reverse transcriptase at codon 184 changing the methionine to either isoleucine or valine (M184V/I).

Zidovudine: HIV‑1 isolates with reduced susceptibility to zidovudine have been selected in cell culture and were also recovered from subjects treated with zidovudine. Genotypic analyses of the isolates selected in cell culture and recovered from zidovudine‑treated subjects showed substitutions in the HIV-1 RT gene resulting in 6 amino acid substitutions (M41L, D67N, K70R, L210W, T215Y or F, and K219Q) that confer zidovudine resistance. In general, higher levels of resistance were associated with greater number of amino acid substitutions.

Cross-Resistance: Cross-resistance has been observed among NRTIs.

Lamivudine Plus Zidovudine: Cross‑resistance between lamivudine and zidovudine has not been reported. In some subjects treated with lamivudine alone or in combination with zidovudine, isolates have emerged with a substitution at codon 184, which confers resistance to lamivudine. Cross-resistance to abacavir, didanosine, tenofovir, and zalcitabine has been observed in some subjects harboring lamivudine‑resistant HIV‑1 isolates. In some subjects treated with zidovudine plus didanosine or zalcitabine, isolates resistant to multiple drugs, including lamivudine, have emerged (see under Zidovudine below).

Lamivudine: See Lamivudine Plus Zidovudine (above).

Zidovudine: In a trial of 167 HIV‑1‑infected subjects, isolates (n = 2) with multi‑drug resistance to didanosine, lamivudine, stavudine, zalcitabine, and zidovudine were recovered from subjects treated for ≥1 year with zidovudine plus didanosine or zidovudine plus zalcitabine. The pattern of resistance‑associated amino acid substitutions with such combination therapies was different (A62V, V75I, F77L, F116Y, Q151M) from the pattern with zidovudine monotherapy, with the Q151M substitution being most commonly associated with multi‑drug resistance. The substitution at codon 151 in combination with substitutions at 62, 75, 77, and 116 results in a virus with reduced susceptibility to didanosine, lamivudine, stavudine, zalcitabine, and zidovudine. Thymidine analogue mutations (TAMs) are selected by zidovudine and confer cross‑resistance to abacavir, didanosine, stavudine, tenofovir, and zalcitabine.

13 NONCLINICAL TOXICOLOGY

13.1 Carcinogenesis, Mutagenesis, Impairment of Fertility

Carcinogenicity: Lamivudine: Long-term carcinogenicity studies with lamivudine in mice and rats showed no evidence of carcinogenic potential at exposures up to 10 times (mice) and 58 times (rats) those observed in humans at the recommended therapeutic dose for HIV-1 infection.

Zidovudine: Zidovudine was administered orally at 3 dosage levels to separate groups of mice and rats (60 females and 60 males in each group). Initial single daily doses were 30, 60, and 120 mg/kg/day in mice and 80, 220, and 600 mg/kg/day in rats. The doses in mice were reduced to 20, 30, and 40 mg/kg/day after day 90 because of treatment-related anemia, whereas in rats only the high dose was reduced to 450 mg/kg/day on day 91 and then to 300 mg/kg/day on day 279.

In mice, 7 late-appearing (after 19 months) vaginal neoplasms (5 nonmetastasizing squamous cell carcinomas, 1 squamous cell papilloma, and 1 squamous polyp) occurred in animals given the highest dose. One late-appearing squamous cell papilloma occurred in the vagina of a middle-dose animal. No vaginal tumors were found at the lowest dose.

In rats, 2 late-appearing (after 20 months), nonmetastasizing vaginal squamous cell carcinomas occurred in animals given the highest dose. No vaginal tumors occurred at the low or middle dose in rats. No other drug-related tumors were observed in either sex of either species.

At doses that produced tumors in mice and rats, the estimated drug exposure (as measured by AUC) was approximately 3 times (mouse) and 24 times (rat) the estimated human exposure at the recommended therapeutic dose of 100 mg every 4 hours.

It is not known how predictive the results of rodent carcinogenicity studies may be for humans.

Mutagenicity: Lamivudine: Lamivudine was mutagenic in an L5178Y/TK+/- mouse lymphoma assay and clastogenic in a cytogenetic assay using cultured human lymphocytes. Lamivudine was negative in a microbial mutagenicity assay, in an in vitro cell transformation assay, in a rat micronucleus test, in a rat bone marrow cytogenetic assay, and in an assay for unscheduled DNA synthesis in rat liver.

Zidovudine: Zidovudine was mutagenic in an L5178Y/TK+/- mouse lymphoma assay, positive in an in vitro cell transformation assay, clastogenic in a cytogenetic assay using cultured human lymphocytes, and positive in mouse and rat micronucleus tests after repeated doses. It was negative in a cytogenetic study in rats given a single dose.

Impairment of Fertility: Lamivudine: In a study of reproductive performance, lamivudine, administered to male and female rats at doses up to 130 times the usual adult dose based on body surface area considerations, revealed no evidence of impaired fertility (judged by conception rates) and no effect on the survival, growth, and development to weaning of the offspring.

Zidovudine: Zidovudine, administered to male and female rats at doses up to 7 times the usual adult dose based on body surface area considerations, had no effect on fertility judged by conception rates.

13.2 Reproductive and Developmental Toxicology Studies

Lamivudine: Reproduction studies have been performed in rats and rabbits at orally administered doses up to 4,000 mg/kg/day and 1,000 mg/kg/day, respectively, producing plasma levels up to approximately 35 times that for the adult HIV dose. No evidence of teratogenicity due to lamivudine was observed. Evidence of early embryolethality was seen in the rabbit at exposure levels similar to those observed in humans, but there was no indication of this effect in the rat at exposure levels up to 35 times those in humans. Studies in pregnant rats and rabbits showed that lamivudine is transferred to the fetus through the placenta.

Zidovudine: Oral teratology studies in the rat and in the rabbit at doses up to 500 mg/kg/day revealed no evidence of teratogenicity with zidovudine. Zidovudine treatment resulted in embryo/fetal toxicity as evidenced by an increase in the incidence of fetal resorptions in rats given 150 or 450 mg/kg/day and rabbits given 500 mg/kg/day. The doses used in the teratology studies resulted in peak zidovudine plasma concentrations (after one half of the daily dose) in rats 66 to 226 times, and in rabbits 12 to 87 times, mean steady-state peak human plasma concentrations (after one sixth of the daily dose) achieved with the recommended daily dose (100 mg every 4 hours). In an in vitro experiment with fertilized mouse oocytes, zidovudine exposure resulted in a dose-dependent reduction in blastocyst formation. In an additional teratology study in rats, a dose of 3,000 mg/kg/day (very near the oral median lethal dose in rats of 3,683 mg/kg) caused marked maternal toxicity and an increase in the incidence of fetal malformations. This dose resulted in peak zidovudine plasma concentrations 350 times peak human plasma concentrations. (Estimated AUC in rats at this dose level was 300 times the daily AUC in humans given 600 mg/day.) No evidence of teratogenicity was seen in this experiment at doses of 600 mg/kg/day or less.

14 CLINICAL STUDIES

There have been no clinical trials conducted with COMBIVIR. See Clinical Pharmacology (12.3) for information about bioequivalence. One COMBIVIR Tablet given twice daily is an alternative regimen to EPIVIR Tablets 150 mg twice daily plus RETROVIR 600 mg per day in divided doses.

14.1 Adults

Lamivudine Plus Zidovudine: The NUCB3007 (CAESAR) trial was conducted using EPIVIR 150‑mg Tablets (150 mg twice daily) and RETROVIR 100‑mg Capsules (2 x 100 mg 3 times daily). CAESAR was a multi‑center, double-blind, placebo-controlled trial comparing continued current therapy (zidovudine alone [62% of subjects] or zidovudine with didanosine or zalcitabine [38% of subjects]) to the addition of EPIVIR or EPIVIR plus an investigational non-nucleoside reverse transcriptase inhibitor, randomized 1:2:1. A total of 1,816 HIV‑1‑infected adults with 25 to 250 (median 122) CD4 cells/mm^3 at baseline were enrolled: median age was 36 years, 87% were male, 84% were nucleoside-experienced, and 16% were therapy‑naive. The median duration on trial was 12 months. Results are summarized in Table 5.

Table 5. Number of Subjects (%) With At Least 1 HIV-1 Disease-Progression Event or Death
Endpoint | Current Therapy (n = 460) | EPIVIR; plus Current Therapy; (n = 896) | EPIVIR; plus a NNRTIa; plus Current Therapy (n = 460)
HIV-1 progression or death | 90 (19.6%) | 86 (9.6%) | 41 (8.9%)
Death | 27 (5.9%) | 23 (2.6%) | 14 (3.0%)
a An investigational non-nucleoside reverse transcriptase inhibitor not approved in the United States.

14.2 Prevention of Maternal-Fetal HIV-1 Transmission

The utility of zidovudine alone for the prevention of maternal-fetal HIV-1 transmission was demonstrated in a randomized, double-blind, placebo-controlled trial conducted in HIV-1-infected pregnant women with CD4+ cell counts of 200 to 1,818 cells/mm^3 (median in the treated group: 560 cells/mm^3) who had little or no previous exposure to zidovudine. Oral zidovudine was initiated between 14 and 34 weeks of gestation (median 11 weeks of therapy) followed by IV administration of zidovudine during labor and delivery. Following birth, neonates received oral zidovudine syrup for 6 weeks. The trial showed a statistically significant difference in the incidence of HIV‑1 infection in the neonates (based on viral culture from peripheral blood) between the group receiving zidovudine and the group receiving placebo. Of 363 neonates evaluated in the trial, the estimated risk of HIV‑1 infection was 7.8% in the group receiving zidovudine and 24.9% in the placebo group, a relative reduction in transmission risk of 68.7%. Zidovudine was well tolerated by mothers and infants. There was no difference in pregnancy-related adverse events between the treatment groups.

16 HOW SUPPLIED/STORAGE AND HANDLING

COMBIVIR Tablets, containing 150 mg lamivudine and 300 mg zidovudine, are white, scored, film-coated, modified-capsule-shaped tablets, debossed on both tablet faces, such that when broken in half, the full “GXFC3” code is present on both halves of the tablet (“GX” on one face and “FC3” on the opposite face of the tablet).

They are supplied by State of Florida DOH Central Pharmacy as follows:

NDC | Strength | Quantity/Form | Color | Source Prod. Code
53808-0895-1 | 150 MG / 300 MG | 30 Tablets in a Blister Pack | WHITE | 49702-202

Store between 2° and 30°C (36° and 86°F).

17 PATIENT COUNSELING INFORMATION

17.1 Advice for the Patient

Neutropenia and Anemia: Patients should be informed that the important toxicities associated with zidovudine are neutropenia and/or anemia. They should be told of the extreme importance of having their blood counts followed closely while on therapy, especially for patients with advanced HIV-1 disease [see Boxed Warning, Warnings and Precautions (5.1)].

Myopathy: Patients should be informed that myopathy and myositis with pathological changes, similar to that produced by HIV-1 disease, have been associated with prolonged use of zidovudine [see Warnings and Precautions (5.2)].

Lactic Acidosis/Hepatomegaly: Patients should be informed that some HIV medicines, including COMBIVIR, can cause a rare, but serious condition called lactic acidosis with liver enlargement (hepatomegaly) [see Warnings and Precautions (5.3)].

HIV-1/HBV Co-infection: Patients co-infected with HIV-1 and HBV should be informed that deterioration of liver disease has occurred in some cases when treatment with lamivudine was discontinued. Patients should be advised to discuss any changes in regimen with their physician [see Warnings and Precautions (5.4)].

Use With Other Lamivudine-, Zidovudine-, and/or Emtricitabine-Containing Products: COMBIVIR should not be coadministered with drugs containing lamivudine, zidovudine, or emtricitabine, including EPIVIR (lamivudine), EPIVIR-HBV (lamivudine), RETROVIR (zidovudine), EPZICOM (abacavir sulfate and lamivudine), TRIZIVIR (abacavir sulfate, lamivudine, and zidovudine), ATRIPLA (efavirenz, emtricitabine, and tenofovir), EMTRIVA (emtricitabine), TRUVADA (emtricitabine and tenofovir), or COMPLERA™ (rilpivirine/emtricitabine/tenofovir) [see Warnings and Precautions (5.5)].

HIV-1/HCV Co-Infection: Patients with HIV-1/HCV co-infection should be informed that hepatic decompensation (some fatal) has occurred in HIV-1/HCV co-infected patients receiving combination antiretroviral therapy for HIV-1 and interferon alfa with or without ribavirin [see Warnings and Precautions (5.6)].

Drug Interactions: Patients should be cautioned about the use of other medications, including ganciclovir, interferon alfa, and ribavirin, which may exacerbate the toxicity of zidovudine [see Drug Interactions (7.3)].

Redistribution/Accumulation of Body Fat: Patients should be informed that redistribution or accumulation of body fat may occur in patients receiving antiretroviral therapy and that the cause and long-term health effects of these conditions are not known at this time [see Warnings and Precautions (5.9)].

Information About HIV-1 Infection: COMBIVIR is not a cure for HIV-1 infection and patients may continue to experience illnesses associated with HIV-1 infection, including opportunistic infections. Patients should remain under the care of a physician when using COMBIVIR.

Patients should be advised to avoid doing things that can spread HIV-1 infection to others.

- Do not share needles or other injection equipment.
- Do not share personal items that can have blood or body fluids on them, like toothbrushes and razor blades.
- Do not have any kind of sex without protection. Always practice safe sex by using a latex or polyurethane condom or other barrier method to lower the chance of sexual contact with semen, vaginal secretions, or blood.
- Do not breastfeed. Lamivudine and zidovudine are excreted in human breast milk. Mothers with HIV-1 should not breastfeed because HIV-1 can be passed to the baby in the breast milk.

Patients should be informed to take all HIV medications exactly as prescribed.

EPIVIR, RETROVIR, EPZICOM, and TRIZIVIR are registered trademarks of ViiV Healthcare.

The other brands listed are trademarks of their respective owners and are not trademarks of ViiV Healthcare. The makers of these brands are not affiliated with and do not endorse ViiV Healthcare or its products.

Manufactured for:

ViiV Healthcare
Research Triangle Park, NC 27709

by GlaxoSmithKline

Research Triangle Park, NC 27709

Lamivudine is manufactured under agreement from
Shire Pharmaceuticals Group plc
Basingstoke, UK

©2013, ViiV Healthcare. All rights reserved.

This Product was Repackaged By:

State of Florida DOH Central Pharmacy
104-2 Hamilton Park Drive
Tallahassee, FL 32304
USA

PACKAGE LABEL

Label Image for 53808-0895
150mg / 300mg